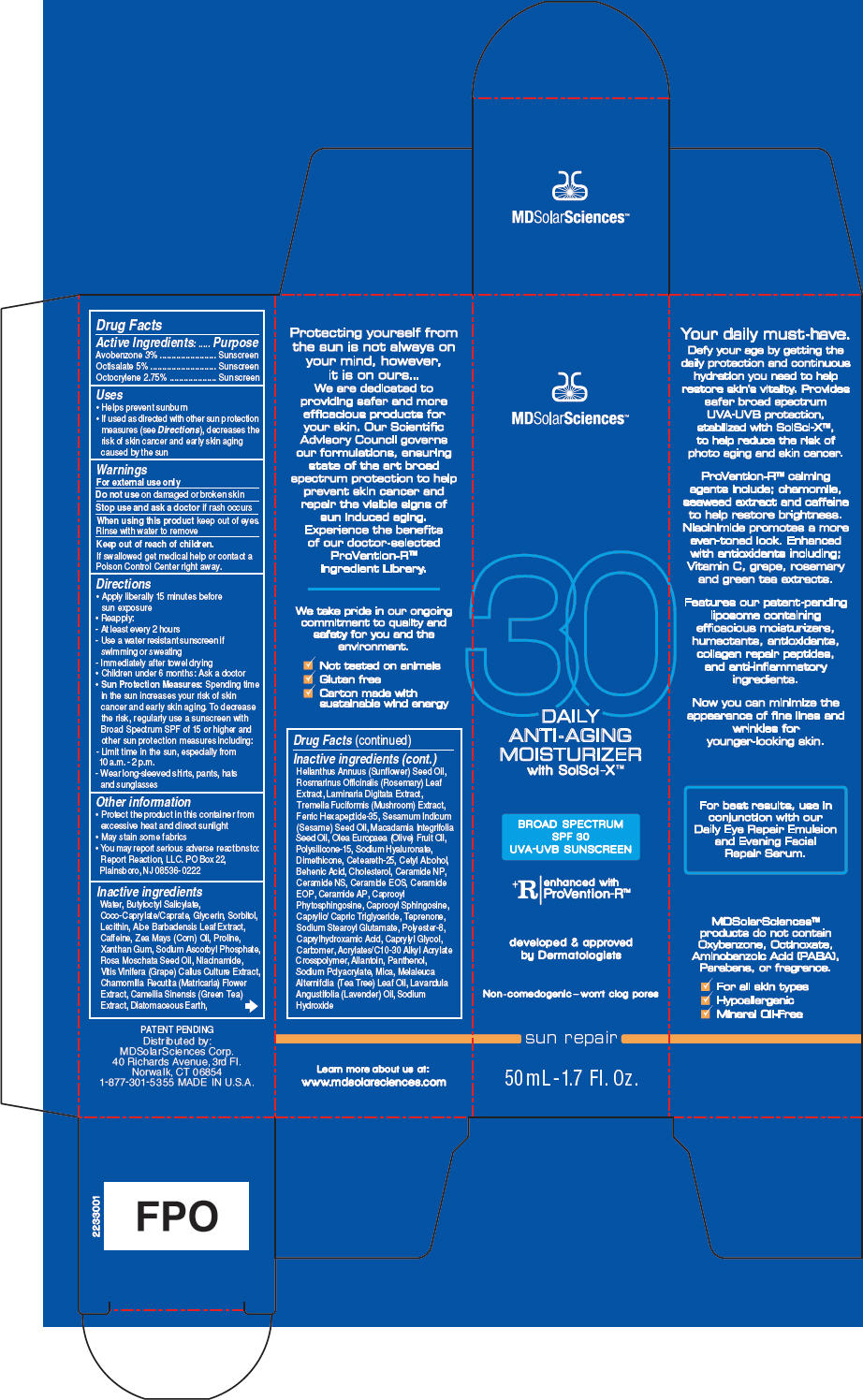 DRUG LABEL: Daily Anti-Aging Moisturizer 
NDC: 49358-555 | Form: LOTION
Manufacturer: MDSolarSciences
Category: otc | Type: HUMAN OTC DRUG LABEL
Date: 20180926

ACTIVE INGREDIENTS: Avobenzone 30 mg/1 mL; Octisalate 50 mg/1 mL; Octocrylene 27.5 mg/1 mL
INACTIVE INGREDIENTS: Water; Butyloctyl Salicylate; Coco-Caprylate/Caprate; Glycerin; Sorbitol; Hydrogenated Soybean Lecithin; Aloe Vera Leaf; Caffeine; Corn Oil; Proline; Xanthan Gum; Sodium Ascorbyl Phosphate; Rosa Moschata Seed Oil; Niacinamide; Vitis Vinifera Seed; Chamomile; Green Tea Leaf; Diatomaceous Earth; Helianthus Annuus Flowering Top; Rosemary; Laminaria Digitata; Tremella Fuciformis Fruiting Body; Acetyl Hexapeptide-8; Sesame Oil; Macadamia Oil; Olive Oil; Polysilicone-15; Hyaluronate Sodium; Dimethicone; Ceteareth-25; Cetyl Alcohol; Behenic Acid; Cholesterol; Ceramide NP; Ceramide NG; 3-Dehydroxy Ceramide 1; Ceramide 9; Ceramide AP; Caprooyl Tetrapeptide-3; N-Hexanoylsphingosine; Medium-Chain Triglycerides; Teprenone; Sodium Stearoyl Glutamate; Polyester-8 (1400 Mw, Cyanodiphenylpropenoyl Capped); Caprylhydroxamic Acid; Caprylyl Glycol; Carbomer Homopolymer Type C (Allyl Pentaerythritol Crosslinked); Carbomer Interpolymer Type A (Allyl Sucrose Crosslinked); Allantoin; Panthenol; Sodium Polyacrylate (8000 MW); Mica; Tea Tree Oil; Lavender Oil; Sodium Hydroxide

Daily Anti-Aging Moisturizer
Broad Spectrum SPF30 Sunscreen UVA-UVB Sunscreen with SolSci-X™

Drug Facts

ACTIVE INGREDIENT

Active Ingredients: | Purpose
Avobenzone 3% | Sunscreen
Octisalate 5% | Sunscreen
Octocrylene 2.75% | Sunscreen

Uses

- Helps prevent sunburn
- If used as directed with other sun protection measures (see Directions), decreases the risk of skin cancer and early skin aging caused by the sun

Warnings

For external use only

Do not use on damaged or broken skin

Stop use and ask a doctor if rash occurs

When using this product keep out of eyes. Rinse with water to remove

Keep out of reach of children.

If swallowed get medical help or contact a Poison Control Center right away.

Directions

- Apply liberally 15 minutes before sun exposure
- Reapply:
  - At least every 2 hours
  - Use a water resistant sunscreen if swimming or sweating
  - Immediately after towel drying
- Children under 6 months: Ask a doctor
- Sun Protection Measures: Spending time in the sun increases your risk of skin cancer and early skin aging. To decrease the risk, regularly use a sunscreen with Broad Spectrum SPF of 15 or higher and other sun protection measures including:
  - Limit time in the sun, especially from 10 a.m. - 2 p.m.
  - Wear long-sleeved shirts, pants, hats and sunglasses

Other information

- Protect the product in this container from excessive heat and direct sunlight
- May stain some fabrics
- You may report serious adverse reactions to: Report Reaction, LLC. PO Box 22, Plainsboro, NJ 08536-0222

Inactive ingredients

Water, Butyloctyl Salicylate, Coco-Caprylate/Caprate, Glycerin, Sorbitol, Lecithin, Aloe Barbadensis Leaf Extract, Caffeine, Zea Mays (Corn) Oil, Proline, Xanthan Gum, Sodium Ascorbyl Phosphate, Rosa Moschata Seed Oil, Niacinamide, Vitis Vinifera (Grape) Callus Culture Extract, Chamomilla Recutita (Matricaria) Flower Extract, Camellia Sinensis (Green Tea) Extract, Diatomaceous Earth, Helianthus Annuus (Sunflower) Seed Oil, Rosmarinus Officinalis (Rosemary) Leaf Extract, Laminaria Digitata Extract, Tremella Fuciformis (Mushroom) Extract, Ferric Hexapeptide-35, Sesamum Indicum (Sesame) Seed Oil, Macadamia Integrifolia Seed Oil, Olea Europaea (Olive) Fruit Oil, Polysilicone-15, Sodium Hyaluronate, Dimethicone, Ceteareth-25, Cetyl Alcohol, Behenic Acid, Cholesterol, Ceramide NP, Ceramide NS, Ceramide EOS, Ceramide EOP, Ceramide AP, Caprooyl Phytosphingosine, Caprooyl Sphingosine, Caprylic/ Capric Triglyceride, Teprenone, Sodium Stearoyl Glutamate, Polyester-8, Caprylhydroxamic Acid, Caprylyl Glycol, Carbomer, Acrylates/C10-30 Alkyl Acrylate Crosspolymer, Allantoin, Panthenol, Sodium Polyacrylate, Mica, Melaleuca Alternifolia (Tea Tree) Leaf Oil, Lavandula Angustifolia (Lavender) Oil, Sodium Hydroxide

Distributed by:
MDSolarSciences Corp.
40 Richards Avenue, 3rd Fl.
Norwalk, CT 06854

PRINCIPAL DISPLAY PANEL - 50 mL Bottle Carton

MDSolarSciences™

30

DAILY
ANTI-AGING
MOISTURIZER
with SolSci-X™

BROAD SPECTRUM
SPF 30
UVA-UVB SUNSCREEN

^+R
enhanced with
ProVention-R™

developed & approved
by Dermatologists

Non-comedogenic – won't clog pores

sun repair

50 mL - 1.7 Fl. Oz.